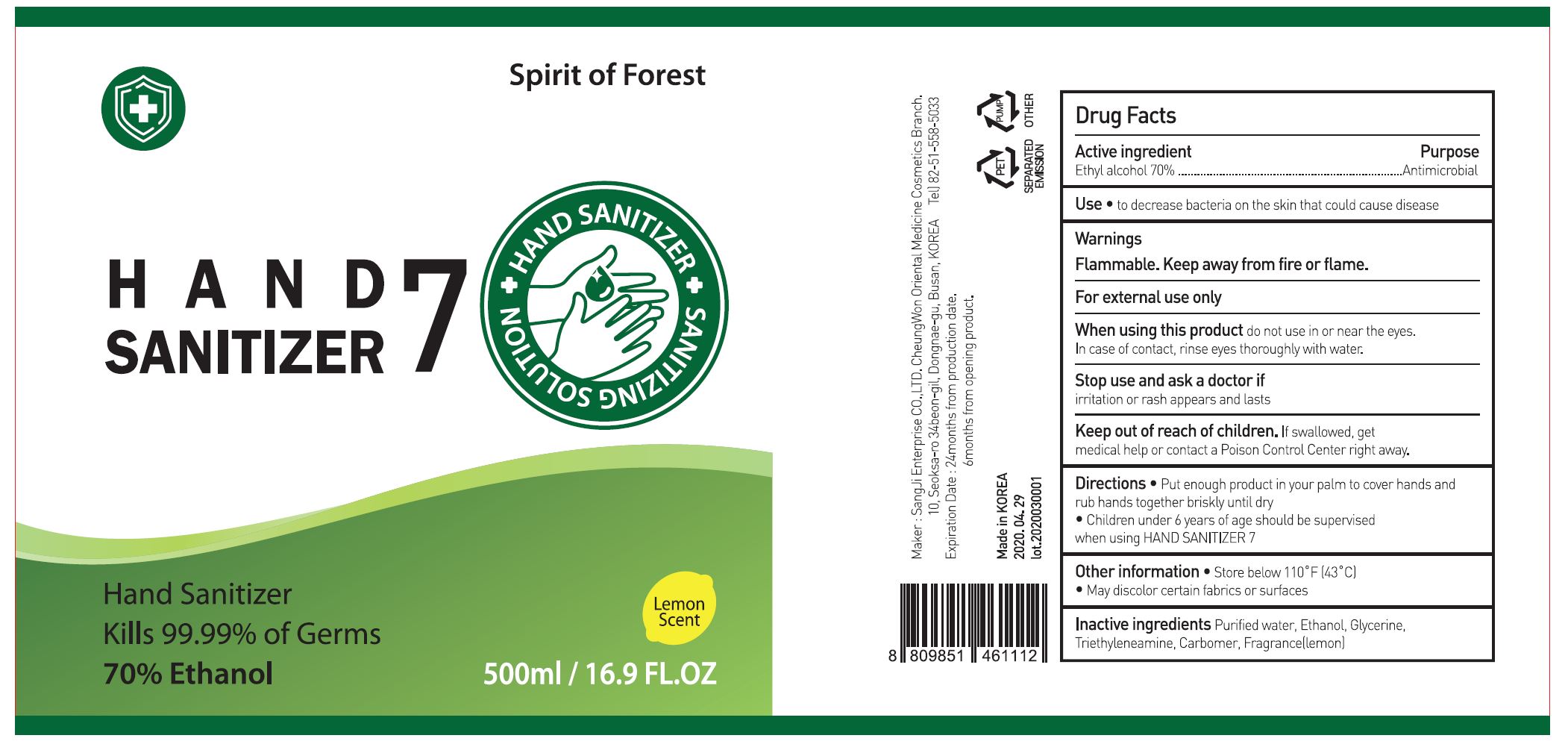 DRUG LABEL: HAND SANITIZER 7
NDC: 75695-0003 | Form: GEL
Manufacturer: Sangji Enterprise Co LTD Cheongwon Oriental Medical Cosmetic Branch
Category: otc | Type: HUMAN OTC DRUG LABEL
Date: 20200516

ACTIVE INGREDIENTS: ALCOHOL 70 mL/100 mL
INACTIVE INGREDIENTS: TROLAMINE; WATER; ALOE VERA LEAF; CARBOMER 940; LEMON OIL

Drug Facts

ACTIVE INGREDIENT

alcohol

PURPOSE

sterilization of hands, skin and so on

KEEP OUT OF REACH OF THE CHILDREN

INDICATIONS AND USAGE

take appropriate amount on the hand, rub and dry well

WARNINGS

■ Flammable. Keep away from fire or flame.

■ For external use only.

■ Do not use in eyes.

■ lf swallowed, get medical help promptly.

■ Stop use, ask doctor lf irritation occurs.

■ Keep out of reach of children.

DOSAGE AND ADMINISTRATION

for external use only

INACTIVE INGREDIENT

glycerin, carbomer, trolamine, water, lemon fragrance